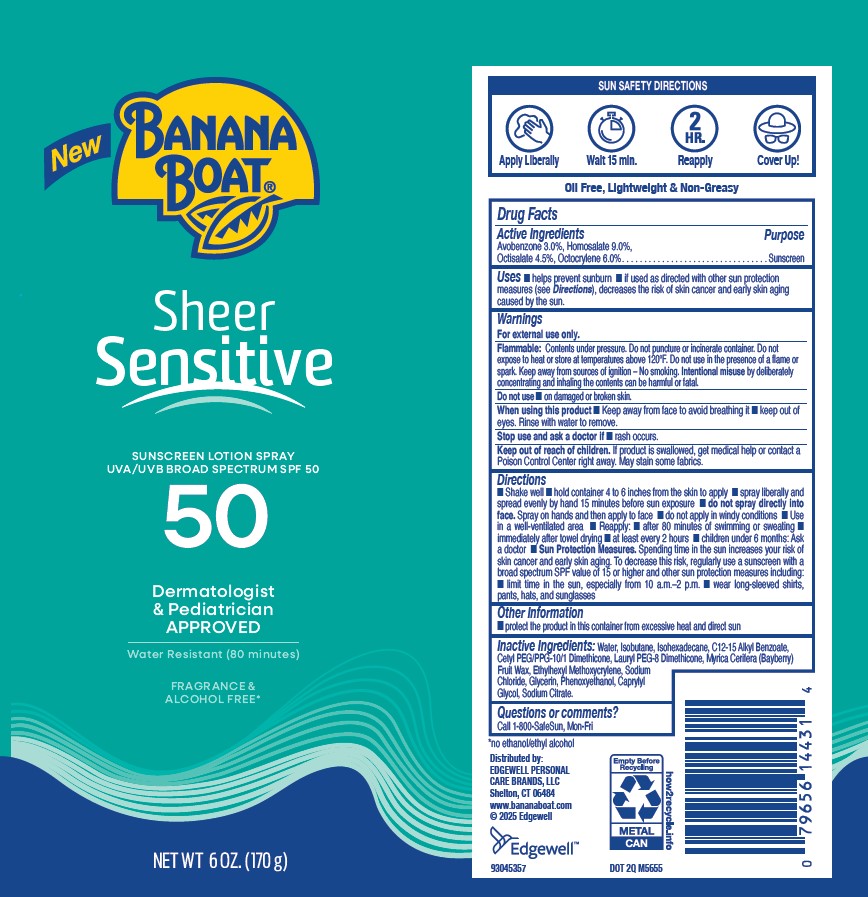 DRUG LABEL: BANANA BOAT
NDC: 63354-842 | Form: AEROSOL
Manufacturer: Edgewell Personal Care Brands LLC
Category: otc | Type: HUMAN OTC DRUG LABEL
Date: 20251203

ACTIVE INGREDIENTS: AVOBENZONE 3 g/100 g; OCTISALATE 4.5 g/100 g; OCTOCRYLENE 6 g/100 g; HOMOSALATE 9 g/100 g
INACTIVE INGREDIENTS: GLYCERIN; C12-15 ALKYL BENZOATE; ISOHEXADECANE; CAPRYLYL GLYCOL; SODIUM CHLORIDE; SODIUM CITRATE; WATER; CETYL PEG/PPG-10/1 DIMETHICONE (HLB 2); LAURYL PEG-8 DIMETHICONE (300 CPS); ETHYLHEXYL METHOXYCRYLENE; ISOBUTANE; MYRICA CERIFERA FRUIT WAX; PHENOXYETHANOL

Active Ingredients

Avobenzone 3.0%, Homosalate 9.0%,Octisalate 4.5%, Octocrylene 6.0%

Purpose

Sunscreen

Uses

■ helps prevent sunburn ■ if used as directed with other sun protection measures (see Directions), decreases the risk of skin cancer and early skin aging caused by the sun.

Warnings

For external use only.

Flammable: Contents under pressure. Do not puncture or incinerate container. Do not expose to heat or store at temperatures above 120°F. Do not use in the presence of a flame or spark. Keep away from sources of ignition – No smoking. Intentional misuse by deliberately concentrating and inhaling the contents can be harmful or fatal.

May stain some fabrics.

Do not use

■ on damaged or broken skin.

When using this product

■ Keep away from face to avoid breathing it ■ keep out of eyes. Rinse with water to remove.

Stop use and ask a doctor if

■ rash occurs.

Keep out of reach of children.

If product is swallowed, get medical help or contact a Poison Control Center right away.

Directions

■ Shake well ■ hold container 4 to 6 inches from the skin to apply ■ spray liberally and spread evenly by hand 15 minutes before sun exposure ■ do not spray directly into face. Spray on hands and then apply to face ■ do not apply in windy conditions ■ Use in a well-ventilated area ■ Reapply: ■ after 80 minutes of swimming or sweating ■ immediately after towel drying ■ at least every 2 hours ■ children under 6 months: Ask a doctor ■ Sun Protection Measures. Spending time in the sun increases your risk of skin cancer and early skin aging. To decrease this risk, regularly use a sunscreen with a broad spectrum SPF value of 15 or higher and other sun protection measures including: ■ limit time in the sun, especially from 10 a.m.–2 p.m. ■ wear long-sleeved shirts,
pants, hats, and sunglasses

Other Information

■ protect the product in this container from excessive heat and direct sun

Inactive Ingredients:

Water, Isobutane, Isohexadecane, C12‐15 Alkyl Benzoate, Cetyl PEG/PPG‐10/1 Dimethicone, Lauryl PEG‐8 Dimethicone, Myrica Cerifera (Bayberry) Fruit Wax, Ethylhexyl Methoxycrylene, Sodium Chloride, Glycerin, Phenoxyethanol, Caprylyl Glycol, Sodium Citrate.

Questions or comments?

Call 1-800-SafeSun, Mon-Fri

Principal Display Panel

New

BANANA BOAT

Sheer

Sensitive

SUNSCREEN LOTION SPRAY

UVA/UVB BROAD SPECTRUM SPF 50

50

Dermatologist

& Pediatrician

APPROVED

Water Resistant (80 minutes)

FRAGRANCE &

ALCOHOL FREE

6 FL. OZ. (170mL)